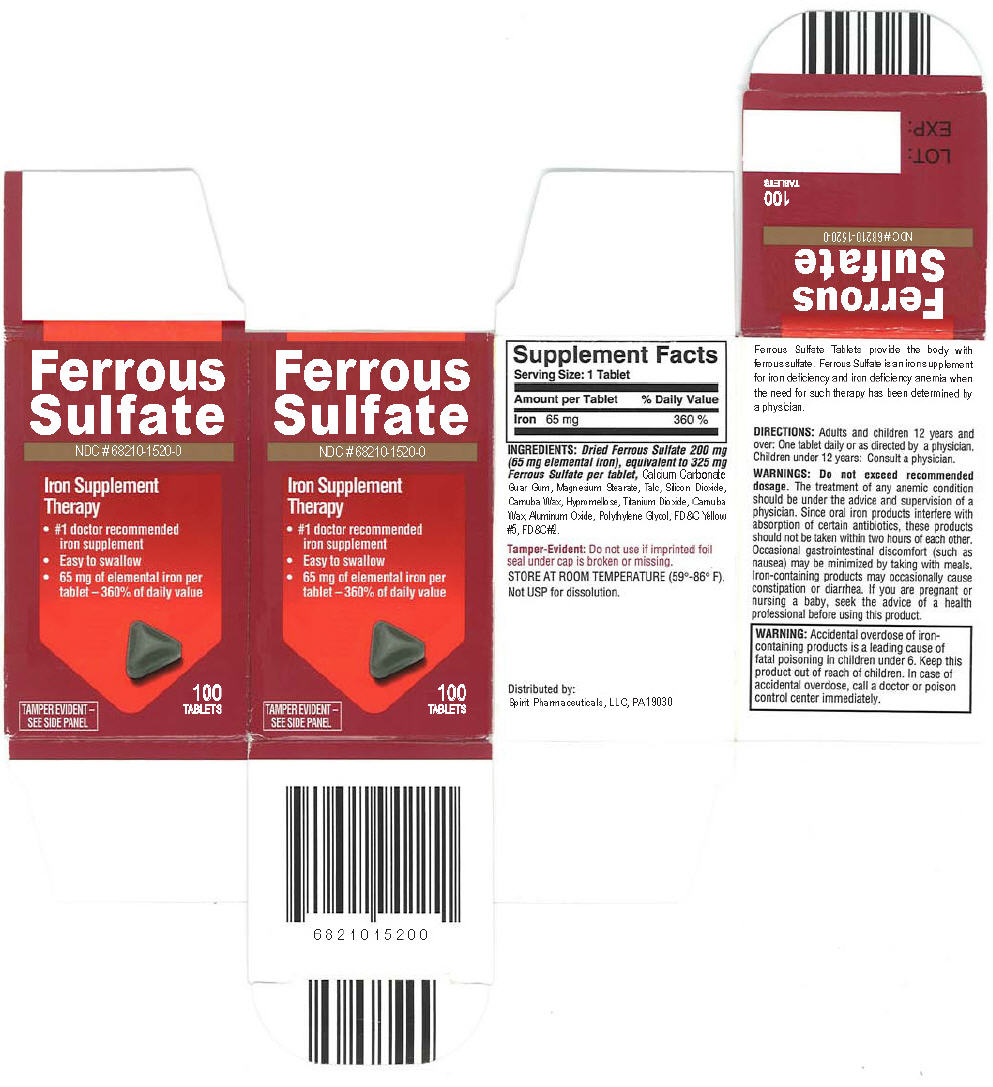 DRUG LABEL: FERROUS SULFATE
NDC: 68210-1520 | Form: TABLET, FILM COATED
Manufacturer: SPIRIT PHARMACEUTICALS,LLC
Category: otc | Type: HUMAN OTC DRUG LABEL
Date: 20101209

ACTIVE INGREDIENTS: FERROUS SULFATE, DRIED 325 mg/1 1
INACTIVE INGREDIENTS: POLYETHYLENE GLYCOL; CALCIUM CARBONATE; GUAR GUM; MAGNESIUM STEARATE; TALC; SILICON DIOXIDE; CARNAUBA WAX; HYPROMELLOSES; TITANIUM DIOXIDE; FD&C YELLOW NO. 5; FD&C BLUE NO. 2; ALUMINUM OXIDE

FERROUS SULFATE TABLETS USP 325 MG

Drug Facts

Active ingredients (in each Caplet)

Dried Ferrous Sulfate 325 mg

Purpose

INDICATIONS AND USAGE

Iron Supplement Therapy

Ferrous Sulphate is an iron supplement for iron deficiency and iron deficiency anemia when the need for such therapy has been determined by a physician.

Warnings

WHEN USING

Do not exceed recommended dosage. The treatment of any anemic condition should be under the advice and supervision of a physician. Since oral iron products interfere with absorption of certain antibiotics, these products should not be taken within tow hours of each other. Occasional gastrointestinal discomfort (such as nausea) may be minimized by taking with meals. Iron-containing products may occasionally cause constipation or diarrhea.

PREGNANCY OR BREAST FEEDING

If are pregnant or nursing a baby, seek the advise of a health professional before using this products.

KEEP OUT OF REACH OF CHILDREN

Warning: Accidental overdose of iron-containing products is a leading cause of fatal poisoning in children under 6. Keep this product out of reach of children. In case of accidental overdose, call a doctor or poison control center immediately.

Direction

- adults and children 12 years and over : take 1 tablet daily or as directed by a doctor
- Children under 12 years : consult a physician..

Other information

- Store at room temperature

Inactive ingredients

Starch USP, Calcium Carbonate USP, Guar Gum , Magnesium Stearate USP, Talc USP, Colloidal Silicon Dioxide USP, , Carnuba Wax

PRINCIPAL DISPLAY PANEL - 65 mg Tablet Carton

Ferrous
Sulfate

NDC # 68210-1520-0

Iron Supplement
Therapy

- #1 doctor recommended
  iron supplement
- Easy to swallow
- 65 mg of elemental iron per
  tablet – 360% of daily value

TAMPER EVIDENT –
SEE SIDE PANEL

100
TABLETS